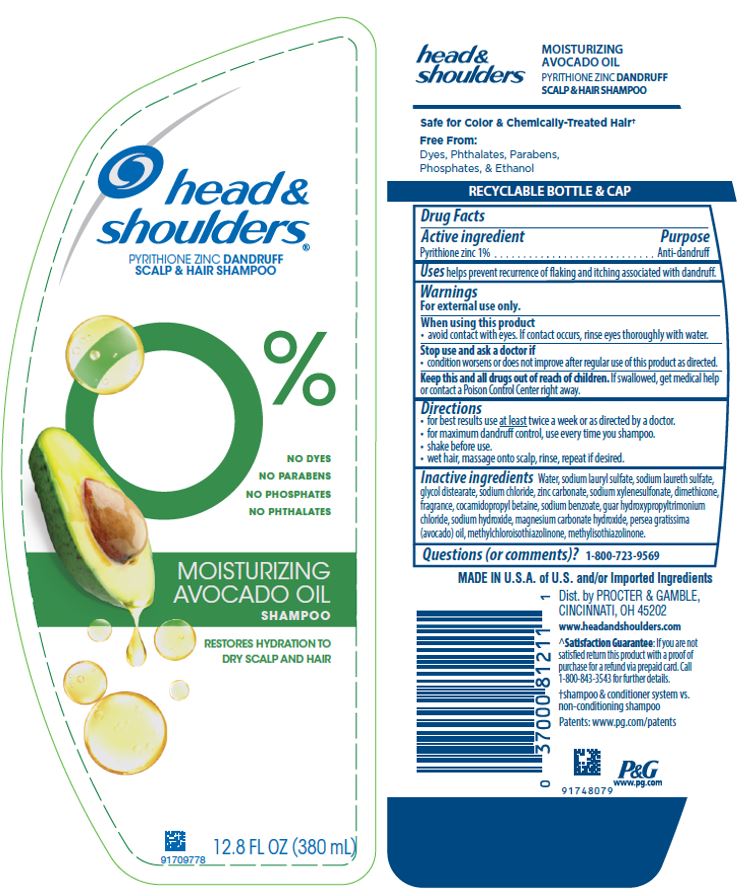 DRUG LABEL: Head and Shoulders Moisturizing Avocado Oil
NDC: 69423-589 | Form: SHAMPOO
Manufacturer: The Procter & Gamble Manufacturing Company
Category: otc | Type: HUMAN OTC DRUG LABEL
Date: 20251218

ACTIVE INGREDIENTS: PYRITHIONE ZINC 1 g/100 mL
INACTIVE INGREDIENTS: SODIUM HYDROXIDE; AVOCADO OIL; SODIUM LAURYL SULFATE; GUAR HYDROXYPROPYLTRIMONIUM CHLORIDE (1.7 SUBSTITUENTS PER SACCHARIDE); WATER; SODIUM LAURETH-3 SULFATE; DIMETHICONE; ZINC CARBONATE; GLYCOL DISTEARATE; SODIUM XYLENESULFONATE; COCAMIDOPROPYL BETAINE; SODIUM CHLORIDE; SODIUM BENZOATE; MAGNESIUM CARBONATE HYDROXIDE; METHYLCHLOROISOTHIAZOLINONE; METHYLISOTHIAZOLINONE

Head and Shoulders® Moisturizing Avocado Oil Shampoo

Drug Facts

Active ingredient

Pyrithione zinc 1%

Purpose

Anti-dandruff

Uses

helps prevent recurrence of flaking and itching associated with dandruff.

Warnings

For external use only.

When using this product

- avoid contact with eyes. If contact occurs, rinse eyes thoroughly with water.

Stop use and ask a doctor if

- condition worsens or does not improve after regular use of this product as directed.

KEEP OUT OF REACH OF CHILDREN

Keep this and all drugs out of reach of children. If swallowed, get medical help or contact a Poison Control Center right away.

Directions

- for best results use at least twice a week or as directed by a doctor.
- for maximum dandruff control, use every time you shampoo.
- shake before use.
- wet hair, massage onto scalp, rinse, repeat if desired.

Inactive ingredients

Water, sodium lauryl sulfate, sodium laureth sulfate, glycol distearate, sodium chloride, zinc carbonate, sodium xylenesulfonate, dimethicone, fragrance, cocamidopropyl betaine, sodium benzoate, guar hydroxypropyltrimonium chloride, sodium hydroxide, magnesium carbonate hydroxide, persea gratissima (avocado) oil, methylchloroisothiazolinone, methylisothiazolinone.

Questions (or comments)?

1-800-723-9569

MADE IN U.S.A. of U.S. and/or Imported Ingredients

Dist. by PROCTER & GAMBLE,
CINCINNATI, OH 45202

PRINCIPAL DISPLAY PANEL - 380 mL Bottle Label

head &
shoulders ®

pyrithione zinc dandruff scalp & hair shampoo

0% NO DYES

NO PARABENS

NO PHOSPHATES

NO PHTHALATES

MOISTURIZING

AVODADO OIL

SHAMPOO

RESTORES HYDRATION TO DRY SCALP AND HAIR

12.8 FL OZ (380 mL)